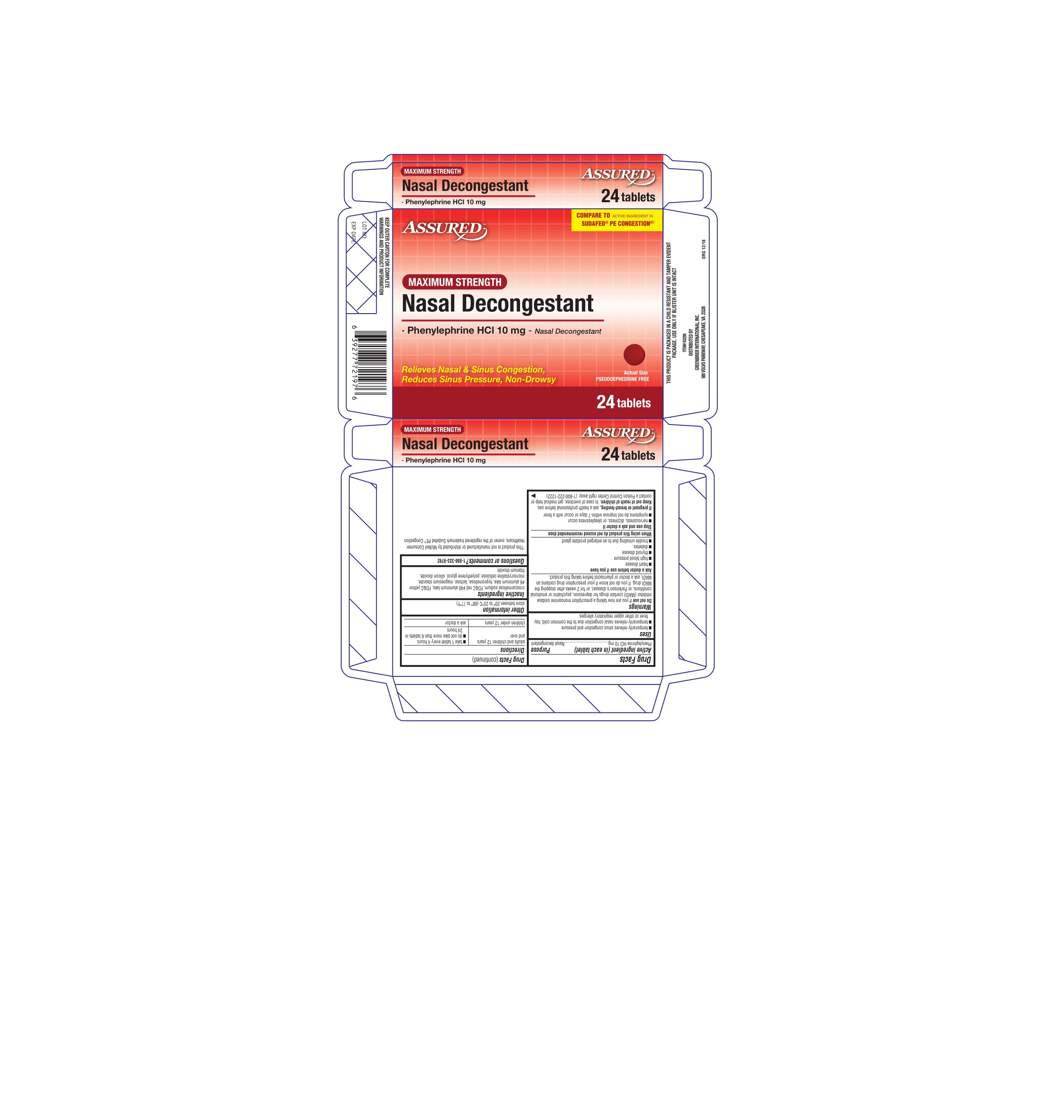 DRUG LABEL: Assured Maximum Strength Nasal Decongestant
NDC: 68210-1180 | Form: TABLET
Manufacturer: Spirit Pharmaceuticals LLC
Category: otc | Type: HUMAN OTC DRUG LABEL
Date: 20211130

ACTIVE INGREDIENTS: PHENYLEPHRINE HYDROCHLORIDE 10 mg/1 1
INACTIVE INGREDIENTS: CROSCARMELLOSE SODIUM; FD&C RED NO. 40; FD&C YELLOW NO. 6; HYPROMELLOSE, UNSPECIFIED; LACTOSE, UNSPECIFIED FORM; MAGNESIUM STEARATE; MICROCRYSTALLINE CELLULOSE; POLYETHYLENE GLYCOL, UNSPECIFIED; SILICON DIOXIDE; TITANIUM DIOXIDE

Assured Maximum Strength Nasal Decongestant 24ct

Drug Facts

Active ingredient (in each tablet)

Phenylephrine HCl 10 mg

Purpose

Nasal decongestant

Uses

■ temporarily relieves sinus congestion and pressure
■ temporarily relieves nasal congestion due to the common cold, hay
fever or other upper respiratory allergies

Warnings

Do not use if you are now taking a prescription monoamine oxidase
inhibitor (MAOI) (certain drugs for depression, psychiatric or emotional
conditions, or Parkinson's disease), or for 2 weeks after stopping the
MAOI drug. If you do not know if your prescription drug contains an
MAOI, ask a doctor or pharmacist before taking this product.

Ask a doctor before use if you have

■ heart disease
■ high blood pressure
■ thyroid disease
■ diabetes
■ trouble urinating due to an enlarged prostate gland

When using this product do not exceed recommended dose

Stop use and ask a doctor if

■ nervousness, dizziness, or sleeplessness occur
■ symptoms do not improve within 7 days or occur with a fever

PREGNANCY OR BREAST FEEDING

If pregnant or breast-feeding, ask a health professional before use.

Keep out of reach of children. In case of overdose, get medical help or
contact a Poison Control Center right away. (1-800-222-1222)

Drug Facts (continued)

Directions

adults and children 12 years and over | ■ take 1 tablet every 4 hours ■ do not take more than 6 tablets in 24 hours
children under 12 years | ask a doctor

Other information

store between 20° to 25°C (68° to 77°F)

Inactive ingredients

croscarmellose sodium, FD&C red #40 aluminum lake, FD&C yellow
#6 aluminum lake, hypromellose, lactose, magnesium stearate,
microcrystalline cellulose, polyethylene glycol, silicon dioxide,
titanium dioxide

Questions or comments? 1-888-333-9792

PRINCIPAL DISPLAY PANEL

ASSURED

COMPARE TO ACTIVE INGREDIENT IN
SUDAFED® PE CONGESTION®†

MAXIMUM STRENGTH

Nasal Decongestant

· Phenylephrine HCl 10 mg - Nasal Decongestant

Relieves Nasal & Sinus Congestion,
Reduces Sinus Pressure, Non-Drowsy

Actual Size

PSEUDOEPHEDRINE FREE

24tablets

†This product is not manufactured or distributed by McNeil Consumer
Healthcare, owner of the registered trademark Sudafed PE® Congestion